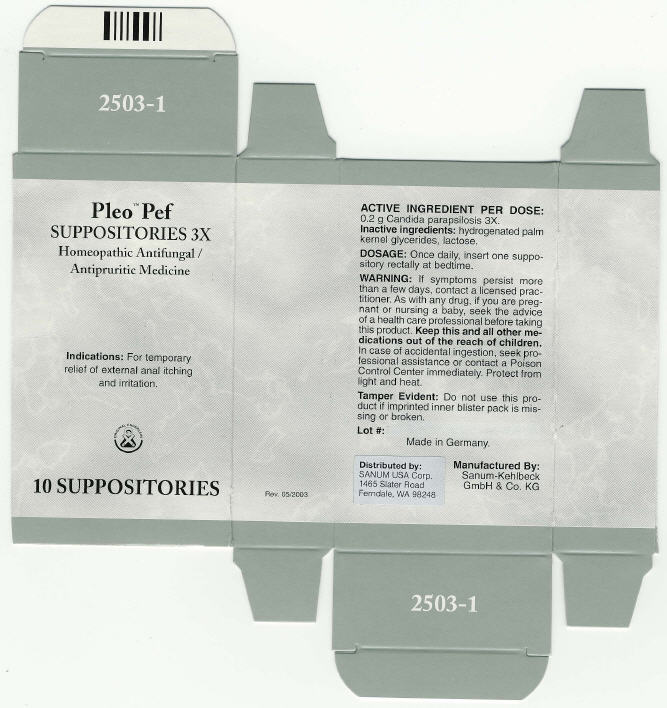 DRUG LABEL: Pleo Pef
NDC: 60681-2503 | Form: SUPPOSITORY
Manufacturer: Sanum Kehlbeck GmbH & Co. KG
Category: homeopathic | Type: HUMAN OTC DRUG LABEL
Date: 20091013

ACTIVE INGREDIENTS: candida parapsilosis 3 [hp_X]/1 1
INACTIVE INGREDIENTS: lactose

Pleo™ Pef
SUPPOSITORIES 3X

Homeopathic Antifungal / Antipruritic Medicine

10 SUPPOSITORIES

Indications

For temporary relief of external anal itching and irritation.

ACTIVE INGREDIENT PER DOSE

0.2 g Candida parapsilosis 3X.

Inactive ingredients

hydrogenated palm kernel glycerides, lactose.

DOSAGE

Once daily, insert one suppository rectally at bedtime.

WARNING

If symptoms persist more than a few days, contact a licensed practitioner. As with any drug, if you are pregnant or nursing a baby, seek the advice of a health care professional before taking this product.

KEEP OUT OF REACH OF CHILDREN

Keep this and all other medications out of the reach of children. In case of accidental ingestion, seek professional assistance or contact a Poison Control Center immediately.

STORAGE AND HANDLING

Protect from light and heat.

Tamper Evident

Do not use this product if imprinted inner blister pack is missing or broken.

Made in Germany.

Distributed by:
SANUM USA Corp.
1465 Slater Road
Ferndale, WA 98248

Manufactured By:
Sanum-Kehlbeck
GmbH & Co. KG

Rev. 05/2003

PRINCIPAL DISPLAY PANEL - 10 Suppositories Carton

Pleo™ Pef
SUPPOSITORIES 3X

Homeopathic Antifungal /
Antipruritic Medicine

Indications: For temporary
relief of external anal itching
and irritation.

ORIGINAL ENDERLEIN

10 SUPPOSITORIES